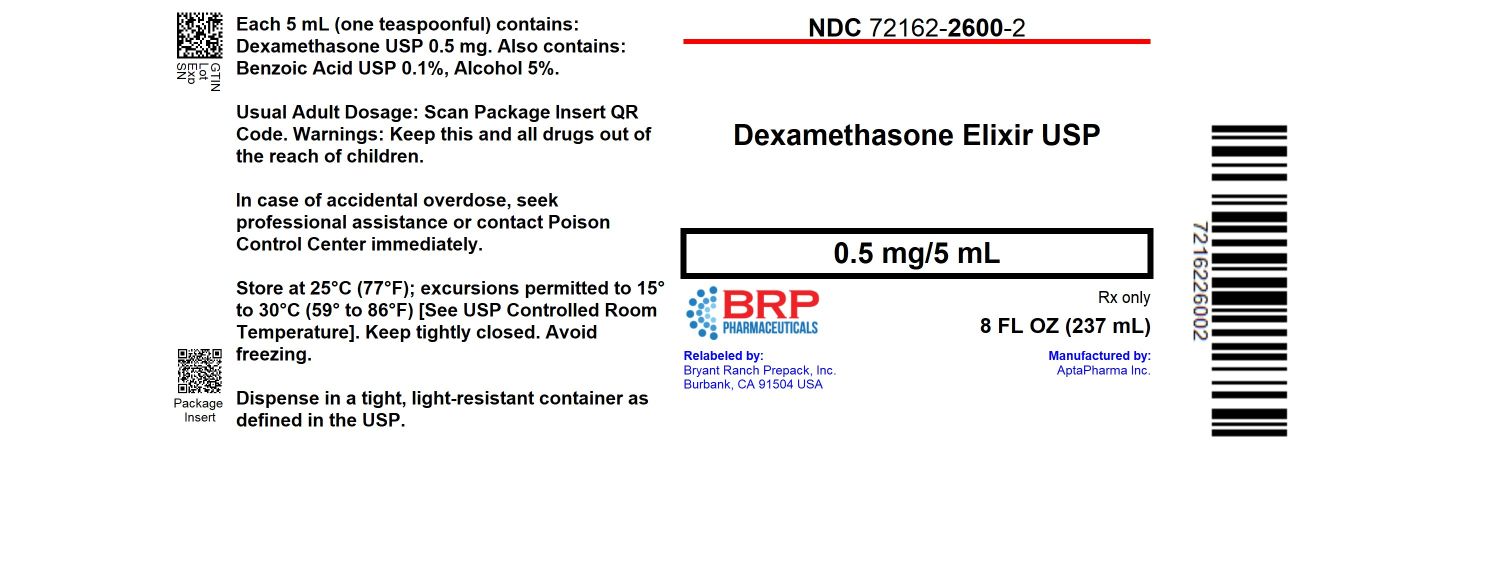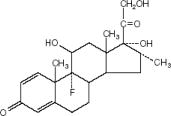 DRUG LABEL: DEXAMETHASONE
NDC: 72162-2600 | Form: ELIXIR
Manufacturer: Bryant Ranch Prepack
Category: prescription | Type: HUMAN PRESCRIPTION DRUG LABEL
Date: 20260109

ACTIVE INGREDIENTS: DEXAMETHASONE 0.5 mg/5 mL
INACTIVE INGREDIENTS: BENZOIC ACID; ALCOHOL; CITRIC ACID MONOHYDRATE; EDETATE DISODIUM; FD&C RED NO. 40; PROPYLENE GLYCOL; WATER; SACCHARIN SODIUM; SORBITOL SOLUTION

DEXAMETHASONE ELIXIR, USP
0.5 mg / 5 mL

DESCRIPTION

Each 5 mL (teaspoonful) contains:
Dexamethasone, USP……………………………………0.5 mg

Also Contains:
Benzoic Acid, USP……………………………………….0.1% (as a preservative)
Alcohol………………………………………………………5%

Inactive Ingredients: Artificial raspberry flavor, citric acid, edetate disodium, FD&C Red #40, propylene glycol, purified water, saccharin sodium, sorbitol solution. Glucocorticoids are adrenocortical steroids, both naturally occurring and synthetic, which are readily absorbed from the gastrointestinal tract.

Dexamethasone, a synthetic adrenocortical steroid, is a white to practically white, odorless, crystalline powder. It is stable in air. It is practically insoluble in water. The molecular weight is 392.47. It is designated chemically as 9-fluoro-11β,17,21-trihydroxy-16α-methylpregna-1,4-diene-3,20-dione. The molecular formula is C22H29FO5 and the structural formula is:

CLINICAL PHARMACOLOGY

Naturally occurring glucocorticoids, (hydrocortisone and cortisone), which also have salt-retaining properties, are used as replacement therapy in adrenocortical deficiency states. Their synthetic analogs, including dexamethasone, are primarily used for their potent antiinflammatory effects in disorders of many organ systems. Glucocorticoids cause profound and varied metabolic effects. In addition, they modify the body’s immune responses to diverse stimuli. At equipotent anti-inflammatory doses, dexamethasone almost completely lacks the sodium-retaining property of hydrocortisone and closely related derivatives of hydrocortisone.

INDICATIONS AND USAGE

Allergic States

Control of severe or incapacitating allergic conditions intractable to adequate trials of conventional treatment: Atopic dermatitis, Bronchial asthma, Contact dermatitis, Drug hypersensitivity reactions, Seasonal or perennial allergic rhinitis, and Serum sickness.

Collagen Diseases

During an exacerbation or as maintenance therapy in selected cases of: Systemic lupus erythematosus, and Acute rheumatic carditis.

Dermatologic Diseases

Bullous dermatitis herpetiformis, Exfoliative dermatitis, Mycosis fungoides, Pemphigus, Severe erythema multiforme (Stevens-Johnson syndrome), Severe psoriasis, and Severe seborrheic dermatitis.

Edematous States

To induce a diuresis or remission of proteinuria in the nephrotic syndrome, without uremia, of the idiopathic type or that due to lupus erythematosus.

Endocrine Disorders

Primary or secondary adrenocortical insufficiency (hydrocortisone or cortisone is the first choice; synthetic analogs may be used in conjunction with mineralocorticoids where applicable; in infancy, mineralocorticoid supplementation is of particular importance), Congenital adrenal hyperplasia, Hypercalcemia associated with cancer, and Nonsuppurative thyroiditis.

Gastrointestinal diseases

To tide the patient over a critical period of the disease in: Ulcerative colitis, and Regional enteritis.

Hematologic Disorders

Idiopathic thrombocytopenic purpura in adults, Secondary thrombocytopenia in adults, Acquired (autoimmune) hemolytic anemia, Erythroblastopenia (RBC anemia), and Congenital (erythroid) hypoplastic anemia.

Miscellaneous

Diagnostic testing of adrenocortical hyperfunction, Tuberculous meningitis with subarachnoid block or impending block when used concurrently with appropriate antituberculous chemotherapy, and Trichinosis with neurologic or myocardial involvement.

Neoplastic Diseases

For palliative management of: Leukemia and lymphomas in adults, and Acute leukemia of childhood.

Ophthalmic Diseases

Severe acute and chronic allergic and inflammatory processes involving the eye and its adnexa, such as: Allergic conjunctivitis, Keratitis, Allergic corneal marginal ulcers, Herpes zoster ophthalmicus, Iritis and iridocyclitis, Chorioretinitis, Anterior segment inflammation, Diffuse posterior uveitis and choroiditis, Optic neuritis, and Sympathetic ophthalmia.

Respiratory Diseases

Symptomatic sarcoidosis, Loeffler's syndrome not manageable by other means, Berylliosis, Fulminating or disseminated pulmonary tuberculosis when used concurrently with appropriate antituberculous chemotherapy, and Aspiration pneumonitis.

Rheumatic Disorders

As adjunctive therapy for short-term administration (to tide the patient over an acute episode or exacerbation) in: Psoriatic arthritis, Rheumatoid arthritis, including juvenile rheumatoid arthritis (selected cases may require low-dose maintenance therapy), Ankylosing spondylitis, Acute and subacute bursitis, Acute nonspecific tenosynovitis, Acute gouty arthritis, Post-traumatic osteoarthritis, Synovitis of osteoarthritis, and Epicondylitis.

CONTRAINDICATIONS

Contraindicated in patients with known systemic fungal infections (See WARNINGS: Infections: Fungal Infections) and patients with a known sensitivity to this drug.

WARNINGS

In patients on corticosteroid therapy subjected to unusual stress, increased dosage of rapidly acting corticosteroids before, during, and after the stressful situation is indicated.

Immunosuppression and Increased Risk of Infection. Corticosteroids, including dexamethasone elixir, suppress the immune system and increase the risk of infection with any pathogen, including viral, bacterial,fungal, protozoan, or helminthic pathogens. Corticosteroids can:

- Reduce resistance to new infections
- Exacerbate existing infections
- Increase the risk of disseminated infections
- Increase the risk of reactivation or exacerbation of latent infections
- Mask some signs of infection

Corticosteroid-associated infections can be mild but can be severe and at times fatal. The rate of infectious complications increases with increasing corticosteroid dosages.

Monitor for the development of infection and consider dexamethasone elixir withdrawal or dosage reduction as needed.

Tuberculosis

If dexamethasone elixir is used to treat a condition in patients with latent tuberculosis or tuberculin reactivity, reactivation of tuberculosis may occur.Closely monitor such patients for reactivation. During prolonged dexamethasone elixir therapy, patients with latent tuberculosis or tuberculin reactivity should receive chemoprophylaxis.

Varicella Zoster and Measles Viral Infections

Varicella and measles can have a serious or even fatal course in non-immune patients taking corticosteroids, including dexamethasone elixir. In corticosteroid-treated patients who have not had these diseases or are nonimmune, particular care should be taken to avoid exposure to varicella and measles:

- If a dexamethasone elixir-treated patient is exposed to varicella, prophylaxis with varicella zoster immune globulin may be indicated. If varicella develops, treatment with antiviral agents may be considered.
- If a dexamethasone elixir-treated patient is exposed to measles, prophylaxis with immunoglobulin may be indicated.

Hepatitis B Virus Reactivation

Hepatitis B virus reactivation can occur in patients who are hepatitis B carriers treated with immunosuppressive dosages of corticosteroids, including dexamethasone elixir. Reactivation can also occur infrequently in corticosteroid-treated patients who appear to have resolved hepatitis B infection.

Screen patients for hepatitis B infection before initiating immunosuppressive (e.g., prolonged) treatment with dexamethasone elixir. For patients who show evidence of hepatitis B infection, recommend consultation with physicians with expertise in managing hepatitis B regarding monitoring and consideration for hepatitis B antiviral therapy.

Fungal Infections

Corticosteroids, including dexamethasone elixir, may exacerbate systemic fungal infections; therefore, avoid dexamethasone elixir use in the presence of such infections unless dexamethasone elixir is needed to control drug reactions. For patients on chronic dexamethasone elixir therapy who develop systemic fungal infections, dexamethasone elixir withdrawal or dosage reduction is recommended.

Amebiasis

Corticosteroids, including dexamethasone elixir, may activate latent amebiasis. Therefore, it is recommended that latent amebiasis or active amebiasis be ruled out before initiating dexamethasone elixir in patients who have spent time in the tropics or patients with unexplained diarrhea.

Strongyloides Infestation

Corticosteroids, including dexamethasone elixir, should be used with great care in patients with known or suspected Strongyloides (threadworm) infestation. In such patients, corticosteroid-induced immunosuppression may lead to Strongyloides hyperinfection and dissemination with widespread larval migration, often accompanied by severe enterocolitis and potentially fatal gram-negative septicemia.

Cerebral Malaria

Avoid corticosteroids, including dexamethasone elixir, in patients with cerebral malaria.

Kaposi’s Sarcoma

Kaposi’s sarcoma has been reported to occur in patients receiving corticosteroid therapy, most often for chronic conditions. Discontinuation of corticosteroids may result in clinical improvement of Kaposi’s sarcoma

Drug-induced secondary adrenocortical insufficiency may result from too rapid withdrawal of corticosteroids and may be minimized by gradual reduction of dosage. This type of relative insufficiency may persist for months after discontinuation of therapy; therefore, in any situation of stress occurring during that period, hormone therapy should be reinstituted. If the patient is receiving steroids already, dosage may have to be increased. Since mineralocorticoid secretion may be impaired, salt and/or a mineralocorticoid should be administered concurrently.

In cerebral malaria, a double-blind trial has shown that the use of corticosteroids is associated with prolongation of coma and a higher incidence of pneumonia and gastrointestinal bleeding.

Prolonged use of corticosteroids may produce posterior subcapsular cataracts, glaucoma with possible damage to the optic nerves, and may enhance the establishment of secondary ocular infections due to fungi or viruses.

Usage in Pregnancy:

Since adequate human reproduction studies have not been done with corticosteroids, use of these drugs in pregnancy or in women of childbearing potential requires that the anticipated benefits be weighed against the possible hazards to the mother and embryo or fetus. Infants born of mothers who have received substantial doses of corticosteroids during pregnancy should be carefully observed for signs of hypoadrenalism.

Corticosteroids appear in breast milk and could suppress growth, interfere with endogenous corticosteroid production, or cause other unwanted effects. Mothers taking pharmacologic doses of corticosteroids should be advised not to nurse.

Average and large doses of hydrocortisone or cortisone can cause elevation of blood pressure, salt and water retention and increased excretion of potassium. These effects are less likely to occur with the synthetic derivatives except when used in large doses. Dietary salt restriction and potassium supplementation may be necessary. All corticosteroids increase calcium excretion.

Administration of live virus vaccines, including smallpox, is contraindicated in individuals receiving immunosuppressive doses of corticosteroids. If inactivated viral or bacterial vaccines are administered to individuals receiving immunosuppressive doses of corticosteroids, the expected serum antibody response may not be obtained. However, immunization procedures may be undertaken in patients who are receiving corticosteroids as replacement therapy, e.g., for Addison's disease.

Literature reports suggest an apparent association between use of corticosteroids and left ventricular free wall rupture after a recent myocardial infarction; therefore, therapy with corticosteroids should be used with great caution in these patients.

PRECAUTIONS

Following prolonged therapy, withdrawal of corticosteroids may result in symptoms of the corticosteroid withdrawal syndrome including fever, myalgia, arthralgia, and malaise. This may occur in patients even without evidence of adrenal insufficiency.

There is an enhanced effect of corticosteroids in patients with hypothyroidism and in those with cirrhosis.

Corticosteroids should be used cautiously in patients with ocular herpes simplex because of possible corneal perforation.

The lowest possible dose of corticosteroid should be used to control the condition under treatment, and when reduction in dosage is possible, the reduction should be gradual.

Psychic derangements may appear when corticosteroids are used, ranging from euphoria, insomnia, mood swings, personality changes, and severe depression, to frank psychotic manifestations. Also, existing emotional instability or psychotic tendencies may be aggravated by corticosteroids.

Aspirin should be used cautiously in conjunction with corticosteroids in hypoprothrombinemia.

Steroids should be used with caution in nonspecific ulcerative colitis, if there is a probability of impending perforation, abscess, or other pyogenic infection, diverticulitis, fresh intestinal anastomoses, active or latent peptic ulcer, renal insufficiency, hypertension, osteoporosis, and myasthenia gravis. Fat embolism has been reported as a possible complication of hypercortisonism.

When large doses are given, some authorities advise that corticosteroids be taken with meals and antacids taken between meals to help to prevent peptic ulcer.

Growth and development of infants and children on prolonged corticosteroid therapy should be carefully observed.

Steroids may increase or decrease motility and number of spermatozoa in some patients.

Phenytoin, phenobarbital, ephedrine, and rifampin may enhance the metabolic clearance of corticosteroids, resulting in decreased blood levels and lessened physiologic activity, thus requiring adjustment in corticosteroid dosage. These interactions may interfere with dexamethasone suppression tests which should be interpreted with caution during administration of these drugs.

False-negative results in the dexamethasone suppression test (DST) in patients being treated with indomethacin have been reported. Thus, results of the DST should be interpreted with caution in these patients.

The prothrombin time should be checked frequently in patients who are receiving corticosteroids and coumarin anticoagulants at the same time because of reports that corticosteroids have altered the response to these anticoagulants. Studies have shown that the usual effect produced by adding corticosteroids is inhibition of response to coumarins, although there have been some conflicting reports of potentiation not substantiated by studies.

When corticosteroids are administered concomitantly with potassium-depleting diuretics, patients should be observed closely for development of hypokalemia.

Information for Patients

Persons who are on immunosuppressant doses of corticosteroids should be warned to avoid exposure to chickenpox or measles. Patients should also be advised that if they are exposed, medical advice should be sought without delay.

ADVERSE REACTIONS

Fluid and Electrolyte Disturbances:

Sodium retention, Fluid retention, Congestive heart failure in susceptible patients, Potassium loss, Hypokalemic alkalosis, and Hypertension.

Musculoskeletal:

Muscle weakness, Steroid myopathy, Loss of muscle mass, Osteoporosis, Vertebral compression fractures, Aseptic necrosis of femoral and humeral heads, Pathologic fracture of long bones, Tendon rupture.

Gastrointestinal:

Peptic ulcer with possible perforation and hemorrhage, Perforation of the small and large bowel, particularly in patients with inflammatory bowel disease, Pancreatitis, Abdominal distention, and Ulcerative esophagitis.

Dermatologic:

Impaired wound healing, Thin fragile skin, Petechiae and ecchymoses, Erythema, Increased sweating, May suppress reactions to skin tests, Other cutaneous reactions, such as allergic dermatitis, urticaria, and angioneurotic edema.

Neurologic:

Convulsions, Increased intracranial pressure with papilledema (pseudotumor cerebri) usually after treatment, Vertigo, Headache, and Psychic disturbances.

Endocrine:

Menstrual irregularities, Development of cushingoid state, Suppression of growth in children, Secondary adrenocortical and pituitary unresponsiveness, particularly in times of stress, as in trauma, surgery, or illness, Decreased carbohydrate tolerance, Manifestations of latent diabetes mellitus, Increased requirements for insulin or oral hypoglycemic agents in diabetics, and Hirsutism.

Ophthalmic:

Posterior subcapsular cataracts, Increased intraocular pressure, Glaucoma, and Exophthalmos.

Metabolic:

Negative nitrogen balance due to protein catabolism

Cardiovascular:

Myocardial rupture following recent myocardial infarction (see WARNINGS)

Other:

Hypersensitivity, Thromboembolism, Weight gain, Increased appetite, Nausea, Malaise, and Hiccups.

OVERDOSAGE

Reports of acute toxicity and/or death following overdosage of glucocorticoids are rare. In the event of overdosage, no specific antidote is available; treatment is supportive and symptomatic.

The oral LD50 of dexamethasone in female mice was 6.5 g/kg.

DOSAGE AND ADMINISTRATION

For oral administration

DOSAGE REQUIREMENTS ARE VARIABLE AND MUST BE INDIVIDUALIZED ON THE BASIS OF THE DISEASE AND THE RESPONSE OF THE PATIENT.

The initial dosage varies from 0.75 to 9 mg a day depending on the disease being treated. In less severe diseases doses lower than 0.75 mg may suffice, while in severe diseases doses higher than 9 mg may be required. The initial dosage should be maintained or adjusted until the patient's response is satisfactory. If satisfactory clinical response does not occur after a reasonable period of time, discontinue dexamethasone elixir and transfer the patient to other therapy.

After a favorable initial response, the proper maintenance dosage should be determined by decreasing the initial dosage in small amounts to the lowest dosage that maintains an adequate clinical response.

Patients should be observed closely for signs that might require dosage adjustment, including changes in clinical status resulting from remissions or exacerbations of the disease, individual drug responsiveness, and the effect of stress (e.g., surgery, infection, trauma). During stress it may be necessary to increase dosage temporarily.

If the drug is to be stopped after more than a few days of treatment, it usually should be withdrawn gradually. The following milligram equivalents facilitate changing to dexamethasone elixir from other glucocorticoids:

DEXAMETHASONE ELIXIR | METHYLPREDNISOLONE AND TRIAMCINOLONE | PREDNISOLONE AND PREDNISONE | HYDROCORTISONE | CORTISONE
0.75 mg = | 4 mg = | 5 mg = | 20 mg = | 25 mg

Dexamethasone suppression tests

1. Tests for Cushing's syndrome
  Give 1 mg of dexamethasone orally at 11:00 p.m. Blood is drawn for plasma cortisol determination at 8:00 a.m. the following morning.
  For greater accuracy, give 0.5 mg of dexamethasone orally every 6 hours for 48 hours. Twenty-four hour urine collections are made for determination of 17-hydroxycorticosteroid excretion.
2. Test to distinguish Cushing's syndrome due to pituitary ACTH excess from Cushing's syndrome due to other causes. Give 2 mg of dexamethasone orally every 6 hours for 48 hours. Twenty-four hour urine collections are made for determination of 17-hydroxycorticosteroid excretion.

HOW SUPPLIED

Dexamethasone Elixir, 0.5 mg dexamethasone per 5 mL, is a clear pink red liquid supplied in the following size:
NDC: 72162-2600-2: 8 fl oz (No Dropper) (237 mL)

RECOMMENDED STORAGE

Store at 25ºC (77ºF); excursions permitted from 15º to 30º C (59º to 86ºF). [see USP Controlled Room Temperature].
KEEP TIGHTLY CLOSED. AVOID FREEZING
Dispense in a tight, light-resistant container as defined in the USP.

To report SUSPECTED ADVERSE REACTIONS, contact Kanchan Healthcare Inc at (833) 845-2624 or kanchan_micc@mitconbiopharma.com or FDA at 1-800-FDA-1088 or www.fda.gov/medwatch

Repackaged/Relabeled by:
Bryant Ranch Prepack, Inc.
Burbank, CA 91504

PACKAGE LABEL

Dexamethasone 0.5mg/5mL Elixir #237